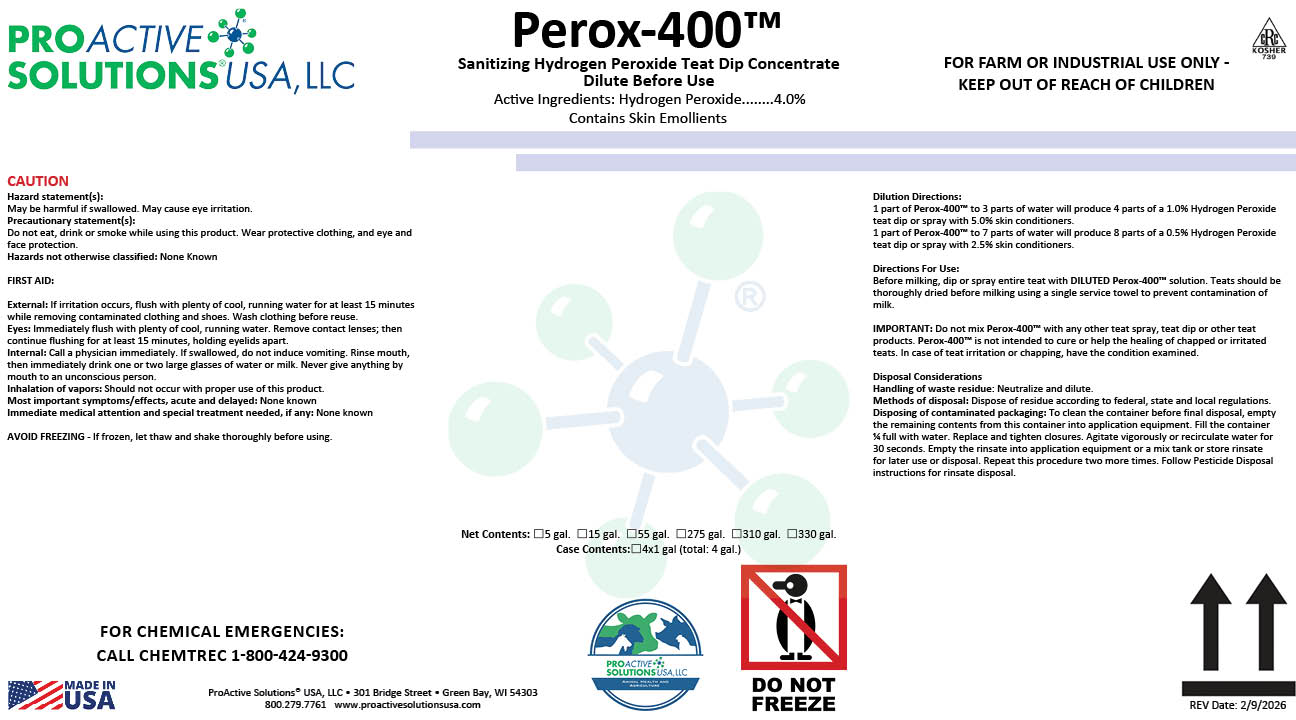 DRUG LABEL: Perox-400
NDC: 63927-4326 | Form: LIQUID
Manufacturer: ProActive Solutions USA, LLC
Category: animal | Type: OTC ANIMAL DRUG LABEL
Date: 20260210

ACTIVE INGREDIENTS: HYDROGEN PEROXIDE 4 kg/100 kg

Perox-400

Perox-400

Dilution Directions:
1 part of Perox-400™ to 3 parts of water will produce 4 parts of a 1.0% Hydrogen Peroxide
teat dip or spray with 5.0% skin conditioners.
1 part of Perox-400™ to 7 parts of water will produce 8 parts of a 0.5% Hydrogen Peroxide
teat dip or spray with 2.5% skin conditioners.
Directions For Use:
Before milking, dip or spray entire teat with DILUTED Perox-400™ solution. Teats should be
thoroughly dried before milking using a single service towel to prevent contamination of
milk.
IMPORTANT: Do not mix Perox-400™ with any other teat spray, teat dip or other teat
products. Perox-400™ is not intended to cure or help the healing of chapped or irritated
teats. In case of teat irritation or chapping, have the condition examined.
Disposal Considerations
Handling of waste residue: Neutralize and dilute.
Methods of disposal: Dispose of residue according to federal, state and local regulations.
Disposing of contaminated packaging: To clean the container before final disposal, empty
the remaining contents from this container into application equipment. Fill the container
¼ full with water. Replace and tighten closures. Agitate vigorously or recirculate water for
30 seconds. Empty the rinsate into application equipment or a mix tank or store rinsate
for later use or disposal. Repeat this procedure two more times. Follow Pesticide Disposal
instructions for rinsate disposal.

Hazard statement(s):
May be harmful if swallowed. May cause eye irritation.
Precautionary statement(s):
Do not eat, drink or smoke while using this product. Wear protective clothing, and eye and
face protection.
Hazards not otherwise classified: None Known
FIRST AID:
External: If irritation occurs, flush with plenty of cool, running water for at least 15 minutes
while removing contaminated clothing and shoes. Wash clothing before reuse.
Eyes: Immediately flush with plenty of cool, running water. Remove contact lenses; then
continue flushing for at least 15 minutes, holding eyelids apart.
Internal: Call a physician immediately. If swallowed, do not induce vomiting. Rinse mouth,
then immediately drink one or two large glasses of water or milk. Never give anything by
mouth to an unconscious person.
Inhalation of vapors: Should not occur with proper use of this product.
Most important symptoms/effects, acute and delayed: None known
Immediate medical attention and special treatment needed, if any: None known
AVOID FREEZING - If frozen, let thaw and shake thoroughly before using.